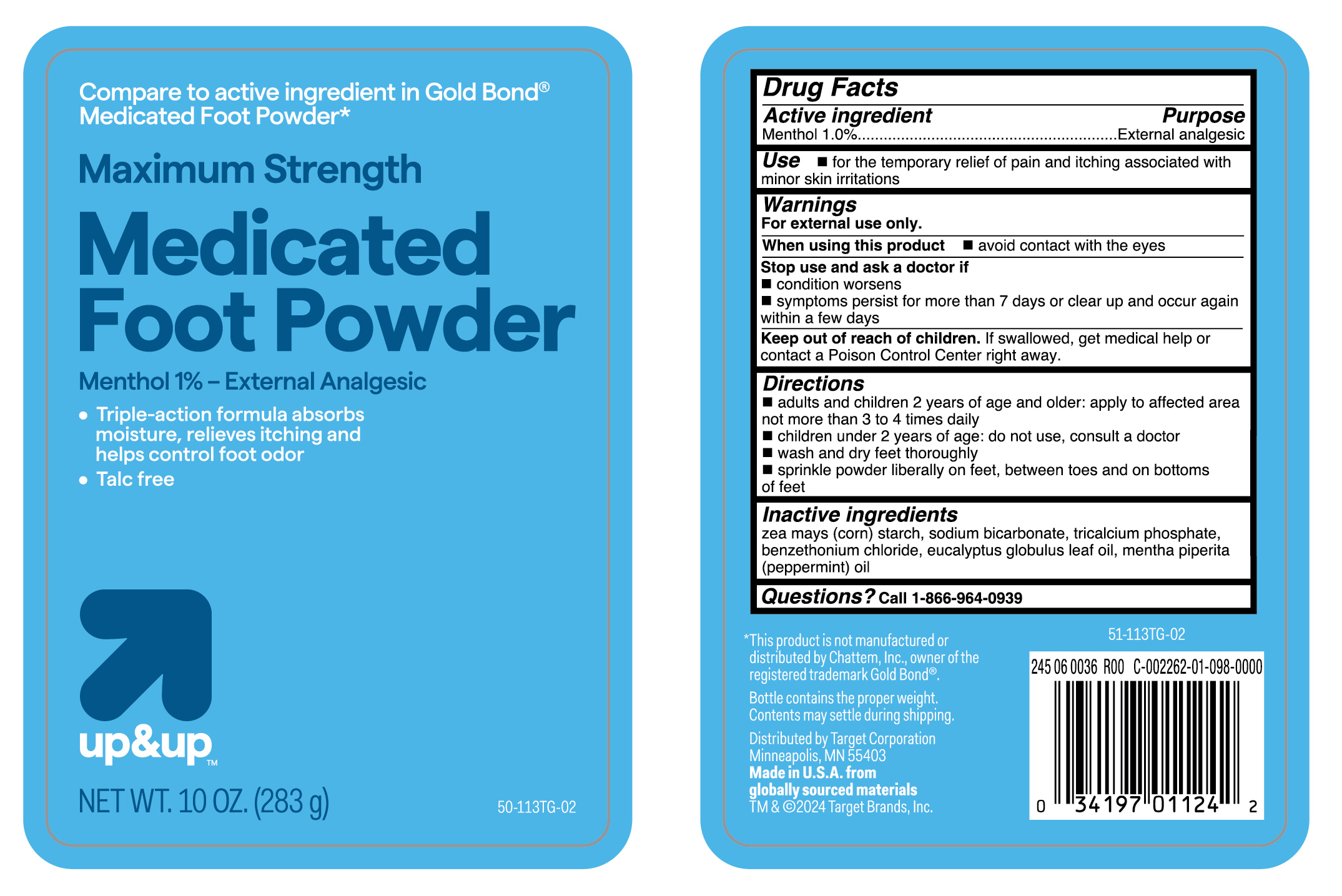 DRUG LABEL: Menthol
NDC: 82442-211 | Form: POWDER
Manufacturer: Target Corporation
Category: otc | Type: HUMAN OTC DRUG LABEL
Date: 20251106

ACTIVE INGREDIENTS: MENTHOL 10 mg/1 g
INACTIVE INGREDIENTS: TRICALCIUM PHOSPHATE; SODIUM BICARBONATE; BENZETHONIUM CHLORIDE; EUCALYPTUS GLOBULUS LEAF OIL; MENTHA PIPERITA (PEPPERMINT) OIL; ZEA MAYS (CORN) STARCH

Medicated Foot Powder -Talc Free

Active ingredient

Menthol 1.0%

Purpose

External analgesic

Use

for the temporary relief of pain and itching associated with minor skin irritations

Warnings

For external use only.

When using this product

- avoid contact with the eyes

Stop use and ask a doctor if

- conditions worsens
- symptoms persists for more than 7 days or clear up and occur again within a few days

Keep out of reach of children.

If swallowed, get medical help or contact a Poison Control Center right away.

Directions

- adults and children 2 years of age and older: apply to affected area not more than 3 to 4 times daily
- children under 2 years of age: do not use, consult a doctor
- wash and dry feet thoroughly
- sprinkle powder liberally on feet, between toes and on bottoms of feet

Inactive ingredients

zea mays (corn) starch, sodium bicarbonate, tricalcium phosphate, benzethonium chloride, eucalyptus globulus leaf oil, mentha piperita (peppermint) oil

Questions?

Call 1-866-964-0939

RECENT MAJOR CHANGES

..

Principal Display Panel

Compare to active ingredient in Gold Bond

Medicated Foot Powder

Maximum Strength

Medicated

Foot Powder

Menthol 1 %- External Analgesic

- Triple- action formula absorbs

moisture, relieves itching and

helps control foot odor

- Talc free

up&up

NET WT. 10 OZ. (283 g)